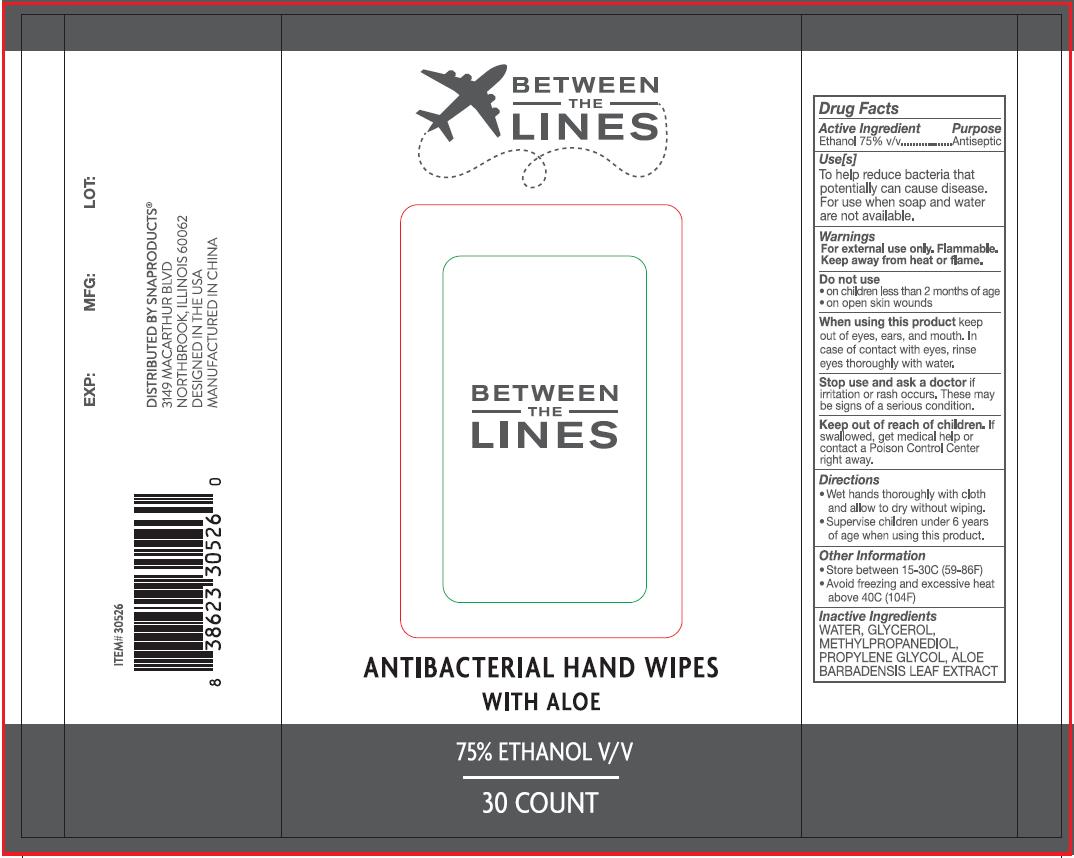 DRUG LABEL: ANTIBACTERIAL HAND WIPES WITH ALOE
NDC: 73992-201 | Form: CLOTH
Manufacturer: Mingshi Technology Co., Ltd.
Category: otc | Type: HUMAN OTC DRUG LABEL
Date: 20200721

ACTIVE INGREDIENTS: ALCOHOL 3.75 mL/1 1
INACTIVE INGREDIENTS: WATER; METHYLPROPANEDIOL; GLYCERIN; PROPYLENE GLYCOL; ALOE VERA LEAF

MingShi, Wipes, 75% Ethanol

Active ingredient

Ethanol 75% v/v. Purpose: Antiseptic

Purpose

Antiseptic

When using this product keep out of eyes, ears, and mouth.

In case of contact with eyes, rinse eyes throughly with water.

Do not use

- on children less than 2 years of age
- or on open skin wounds

STOP USE

Stop using and ask a doctor if irritation or rash occurs. These may be signs of a serious condition.

Keep out of reach of children. If swallowed, get medical help or contact Poison Control Center right away.

Use[s]

To help reduce bacteria that potentially cause disease.

For use when soap and water are not available.

Directions

- Wet hands thoroughly with cloth and allow to dry without wiping.
- Supervise children under 6 years of age when using this product.

Warnings

WARNING FLAMMABLE

Keep away from heat, spark, electrical, fire or flame.

Other information

- Store between 15-30℃ (59-86℉)
- Avoid freezing and excessive heat above 40℃ (104℉)

Inactive Ingredients

WATER, GLYCERIN, METHYLPROPANEDIOL, PROPYLENE GLYCOL, ALOE BAROADENSIS LEAF EXTRACT